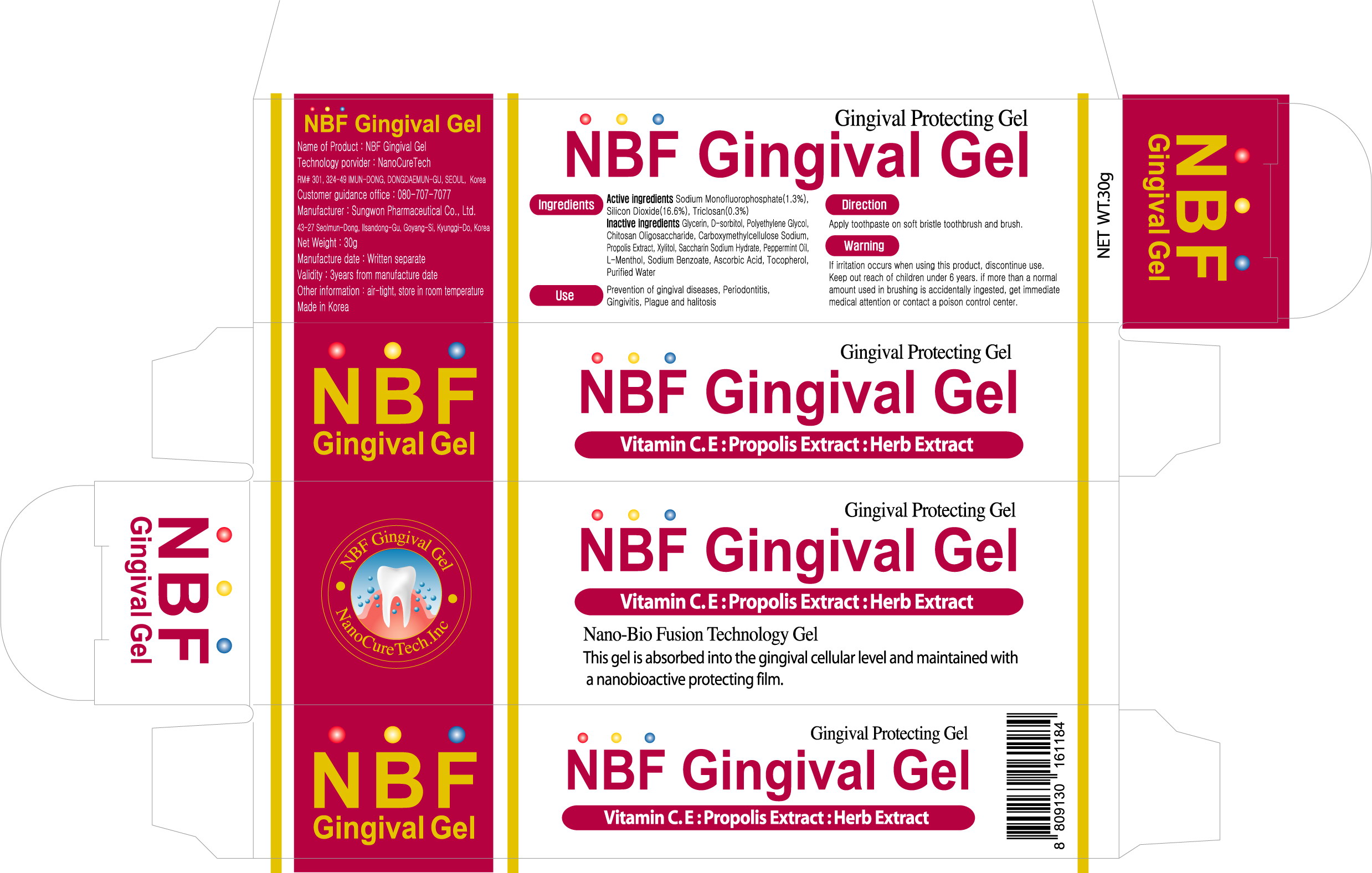 DRUG LABEL: NBF Gingival
NDC: 23636-1001 | Form: GEL
Manufacturer: NanoCureTech
Category: otc | Type: HUMAN OTC DRUG LABEL
Date: 20111111

ACTIVE INGREDIENTS: SODIUM MONOFLUOROPHOSPHATE 0.4 g/30 g
INACTIVE INGREDIENTS: SILICON DIOXIDE; TRICLOSAN; GLYCERIN; SORBITOL; CHITOSAN OLIGOSACCHARIDE; CARBOXYMETHYLCELLULOSE SODIUM; PROPOLIS WAX; XYLITOL; SACCHARIN SODIUM; MENTHA PIPERITA; MENTHOL; SODIUM BENZOATE; ASCORBIC ACID; TOCOPHEROL; WATER

Drug Facts

active ingredient: sodium monofluorophosphate

inactive ingredient: silicon dioxide, triclosan, glycerin, d-sorbitol, polyethylene glycol, chitosan oligosaccharide, carboxymethylcellulose sodium, propolis extract, xylitol, sacccharin sodium hydroate, peppermint oil, l-menthol, sodium benzoate, ascorbic acid, tocopherol, purified water

PURPOSE

■ prevention of gingival disease

keep out of reach of the children

INDICATIONS AND USAGE

apply toothpast on soft bristle toothbrush and brush

WARNINGS

if irritation occurs when using this product, discontinue use

DOSAGE AND ADMINISTRATION

■ apply three times a day after meals